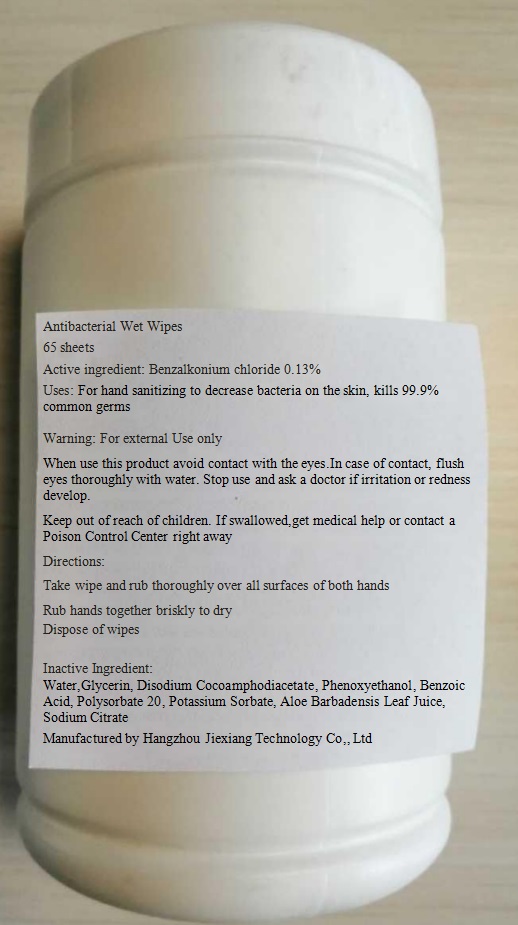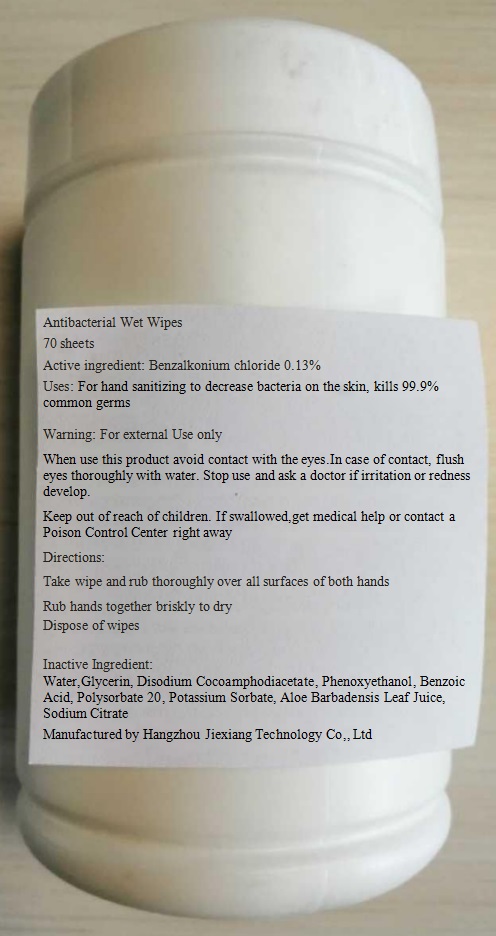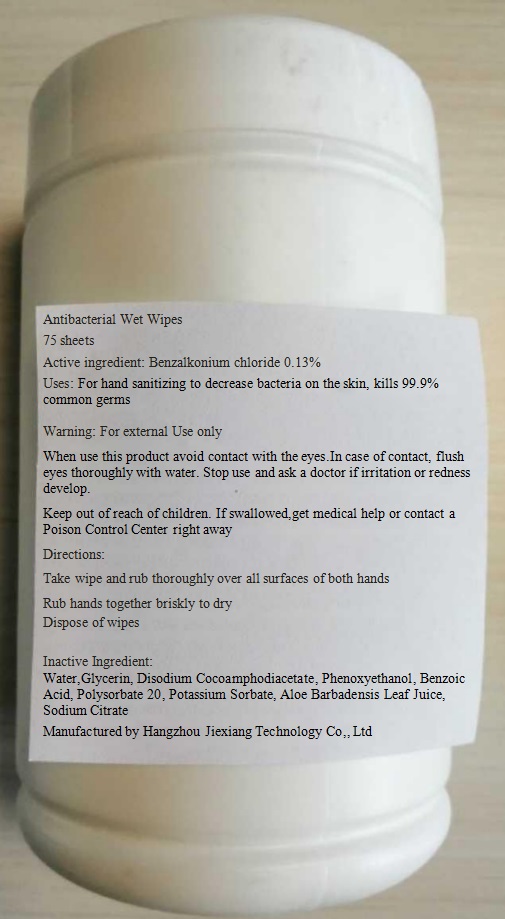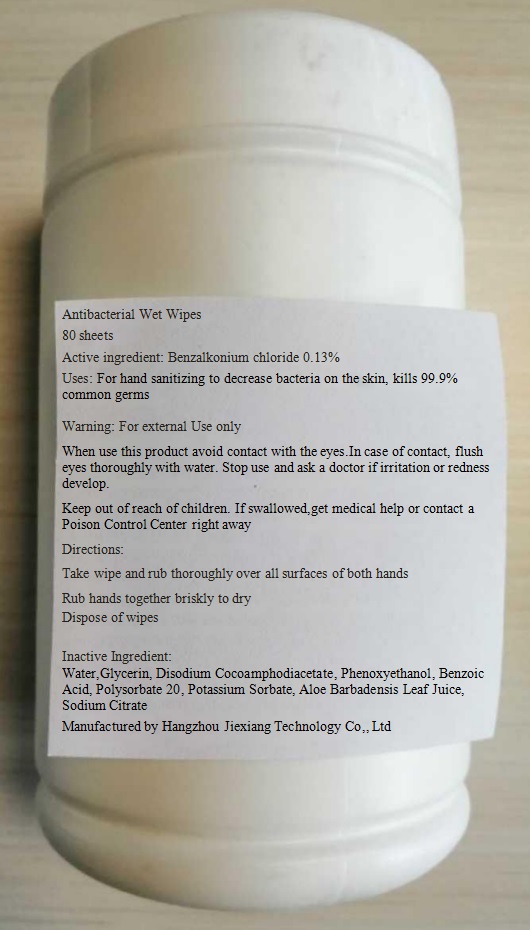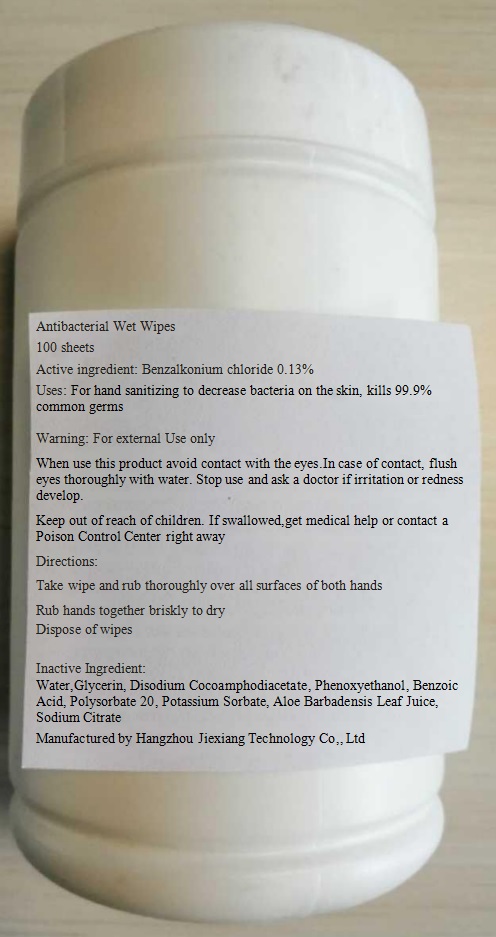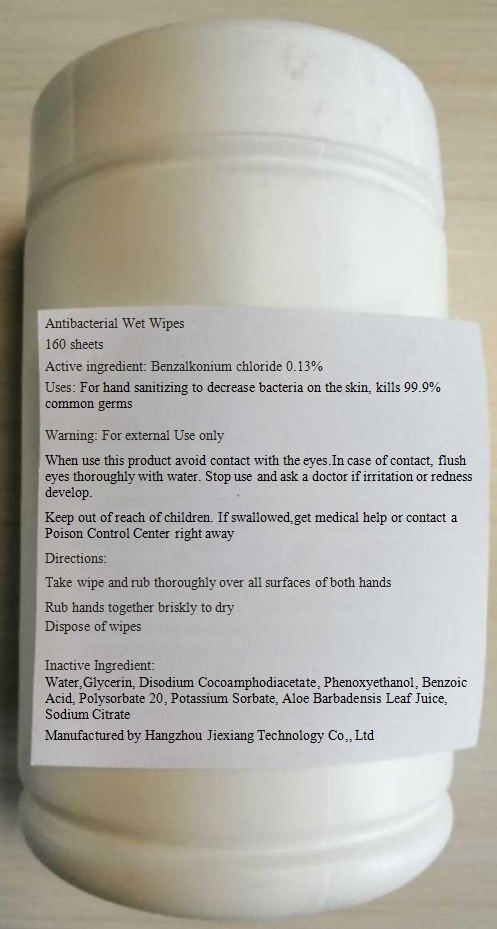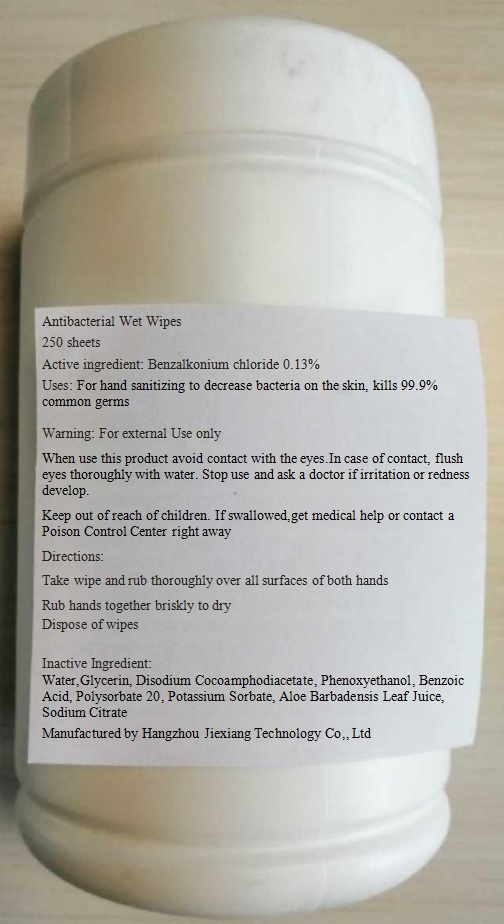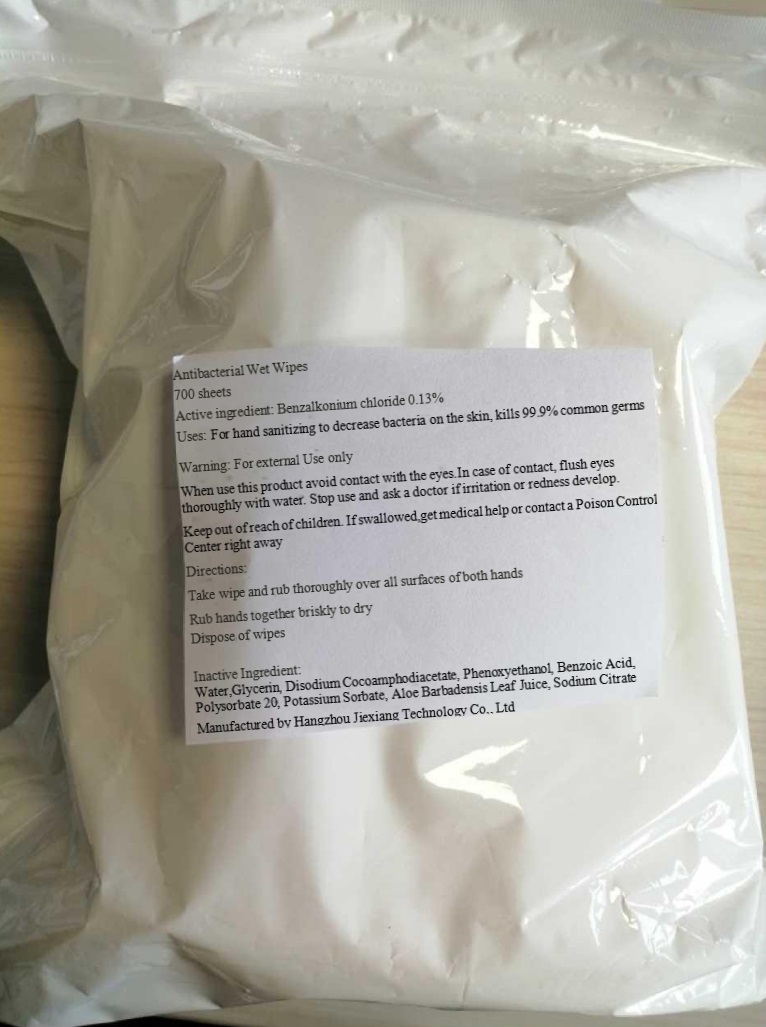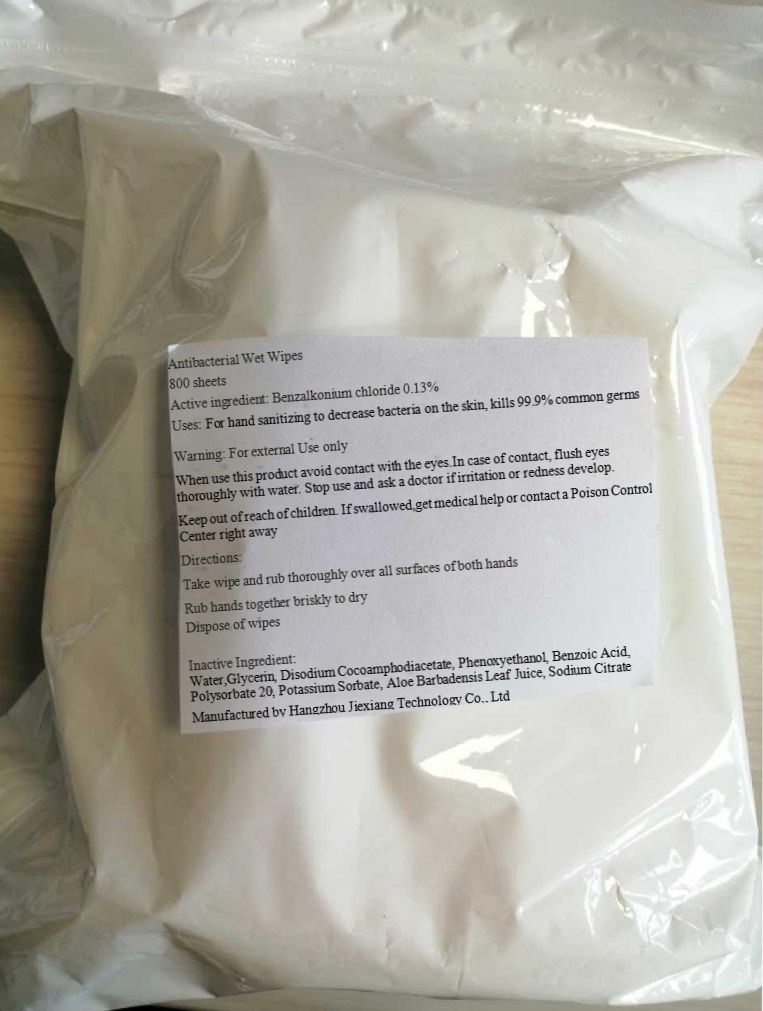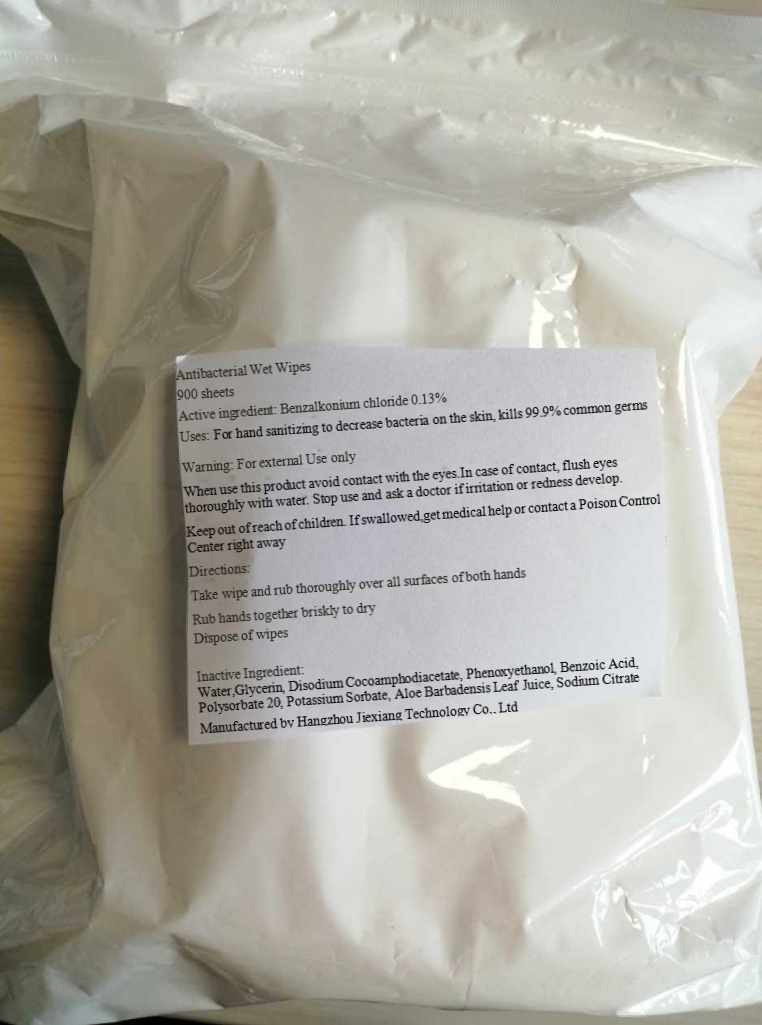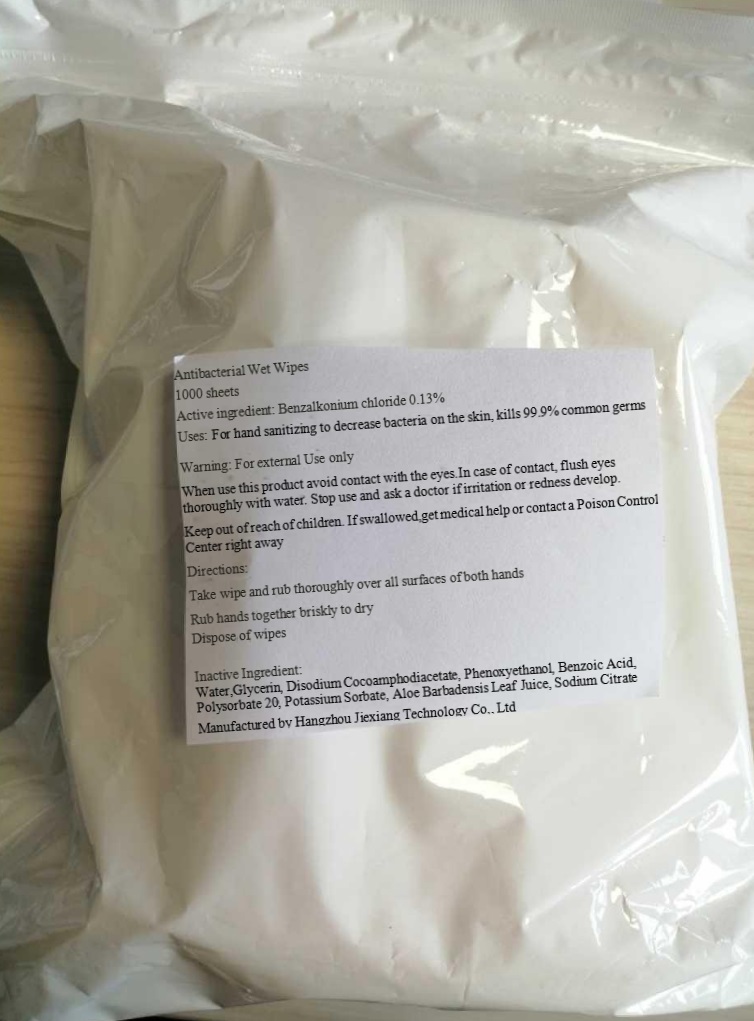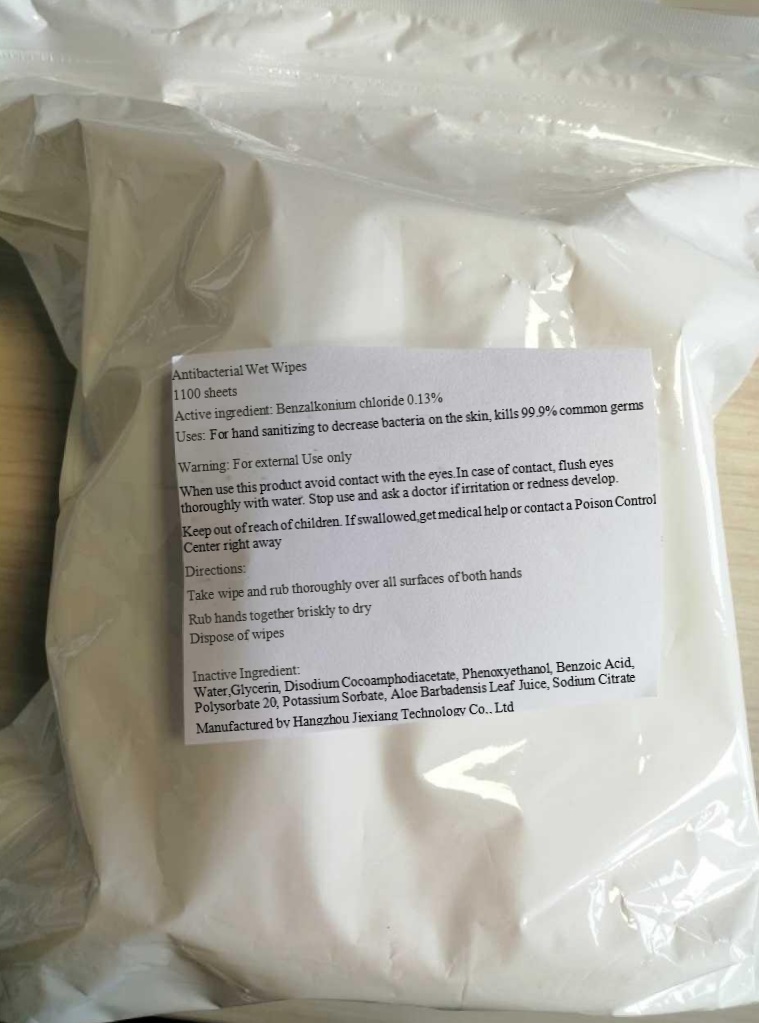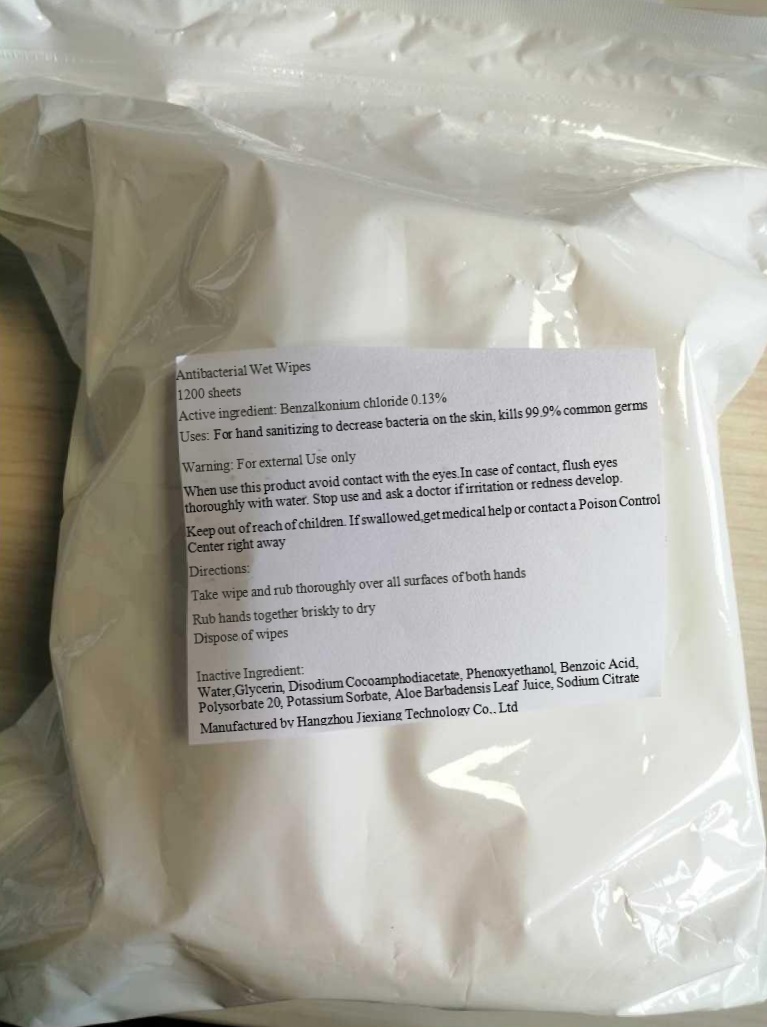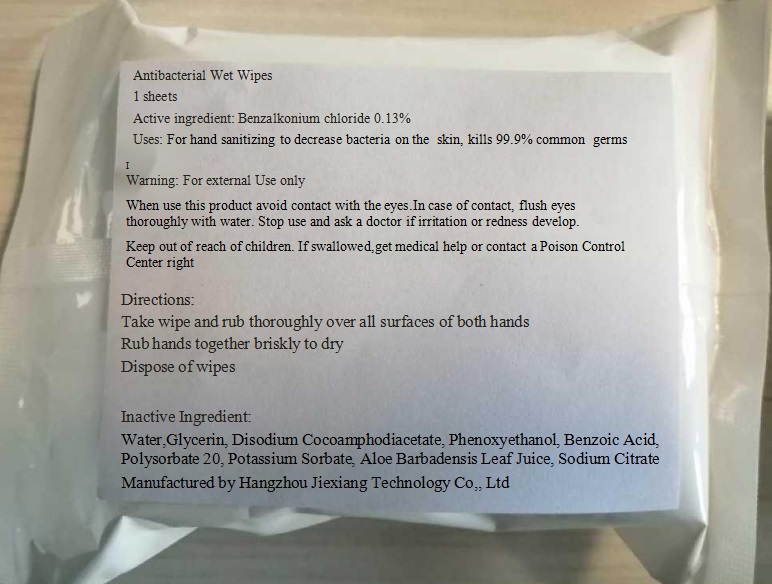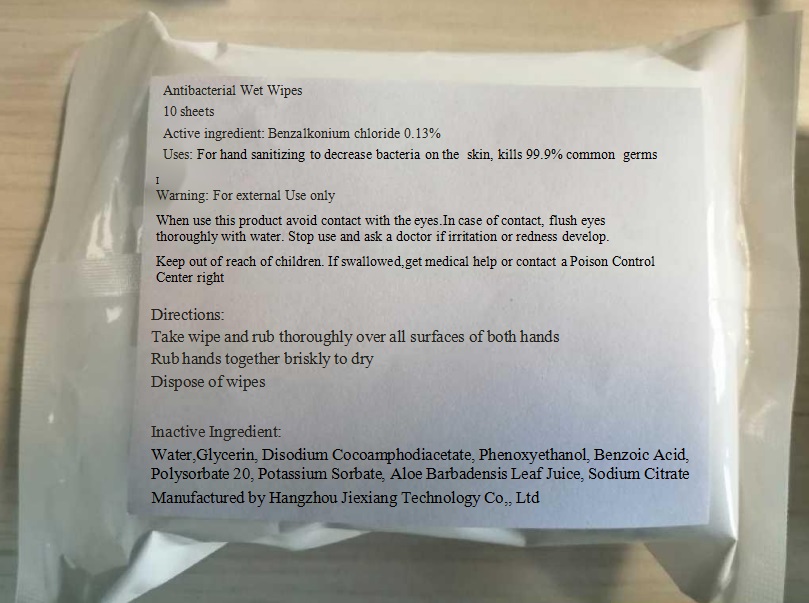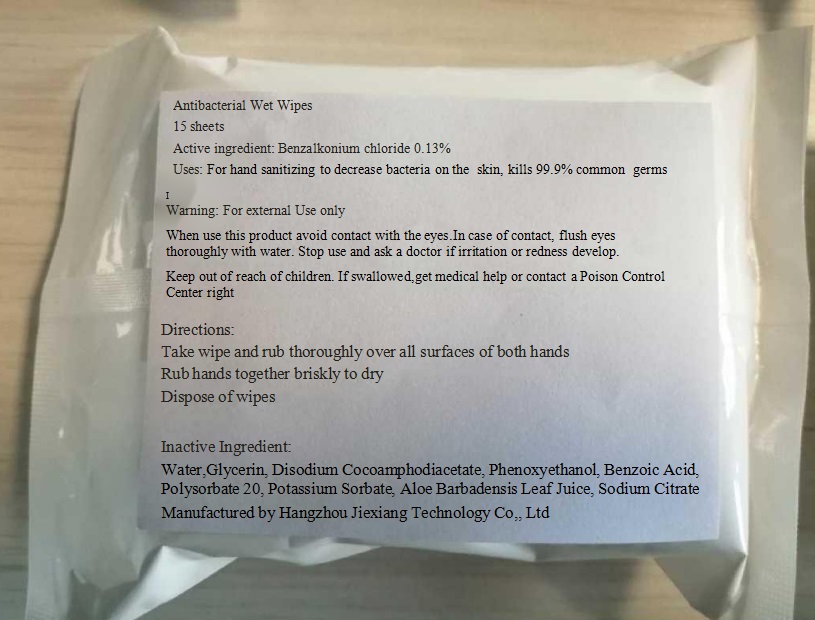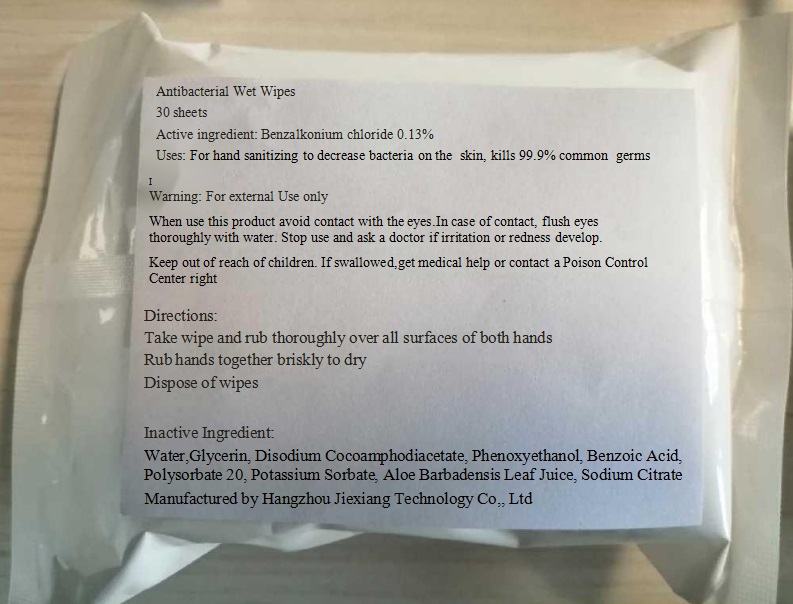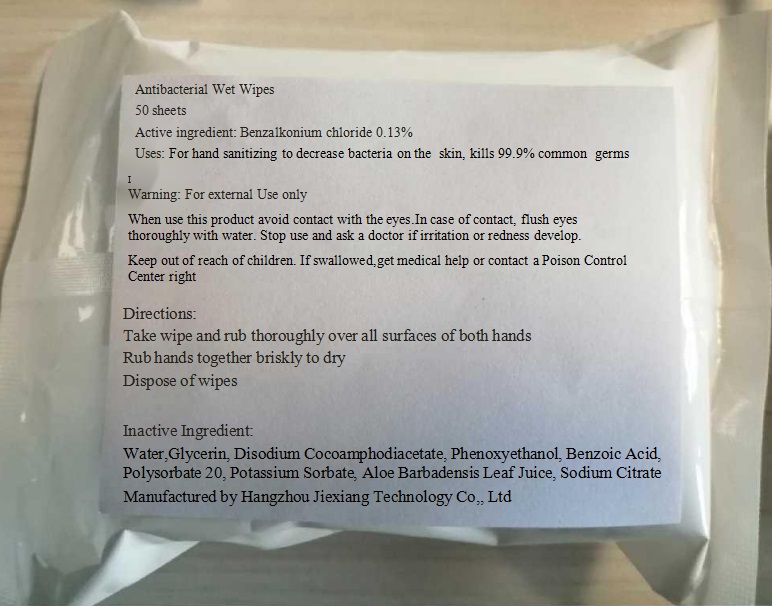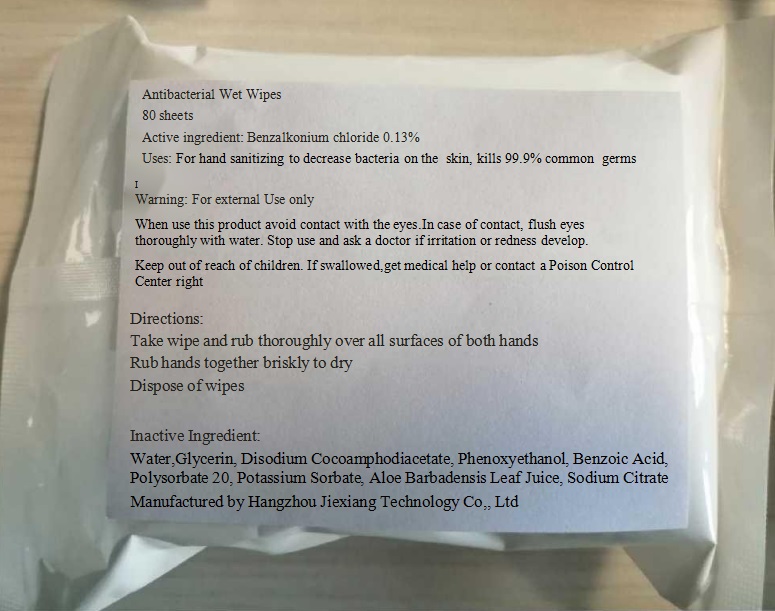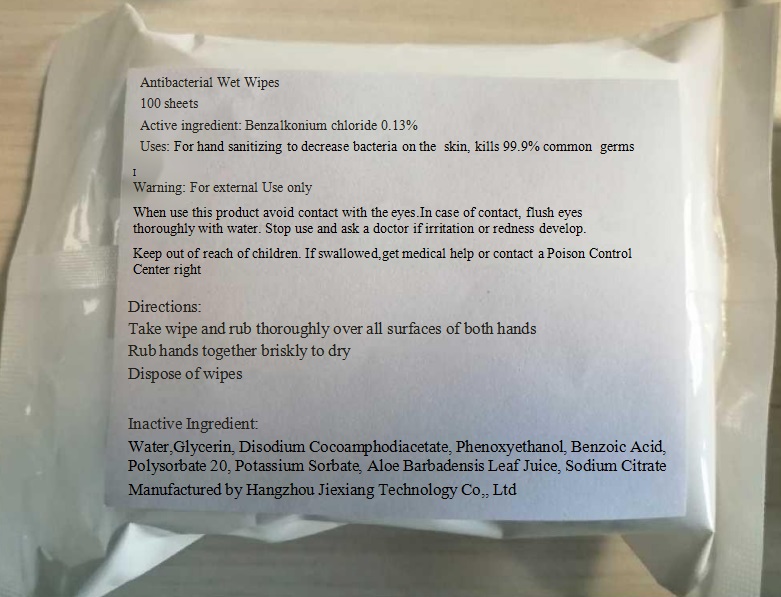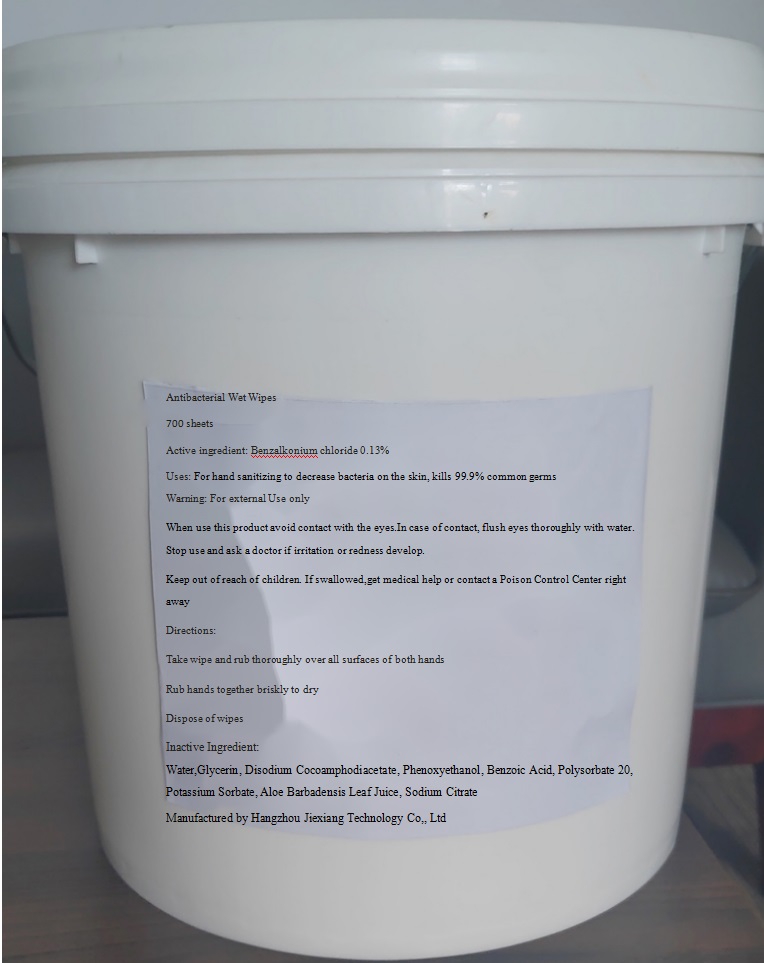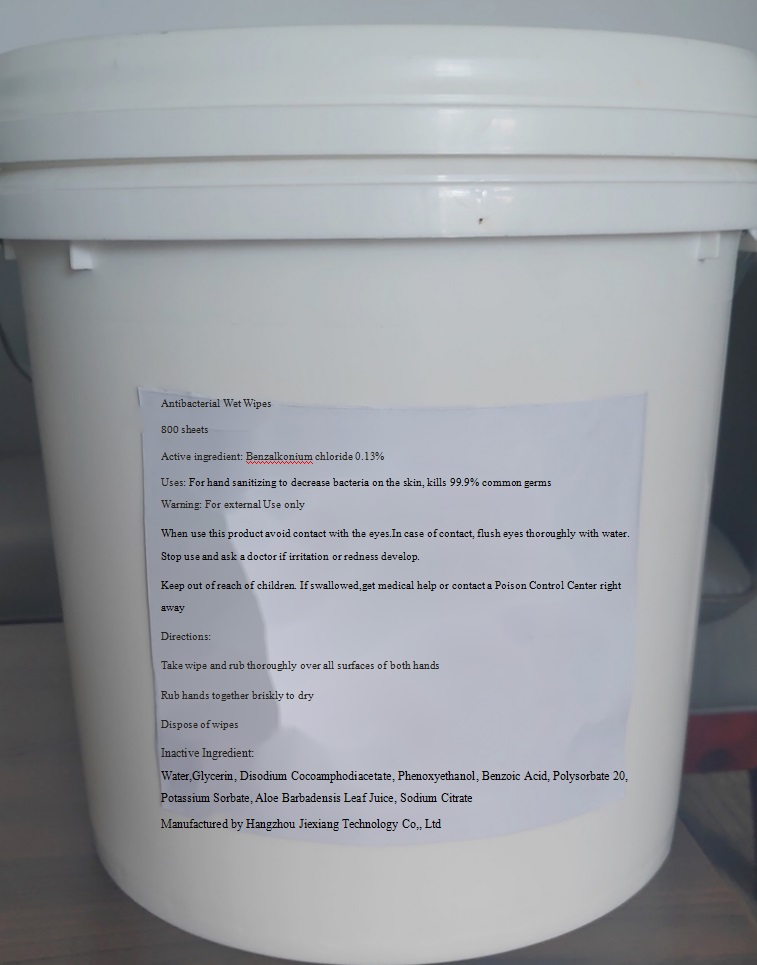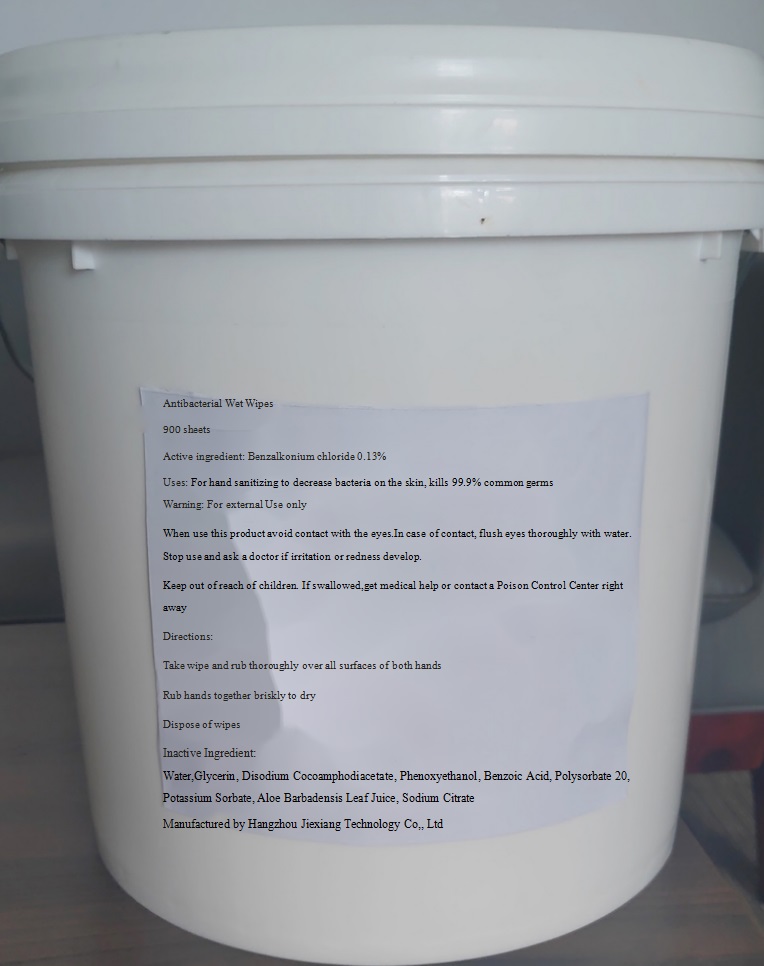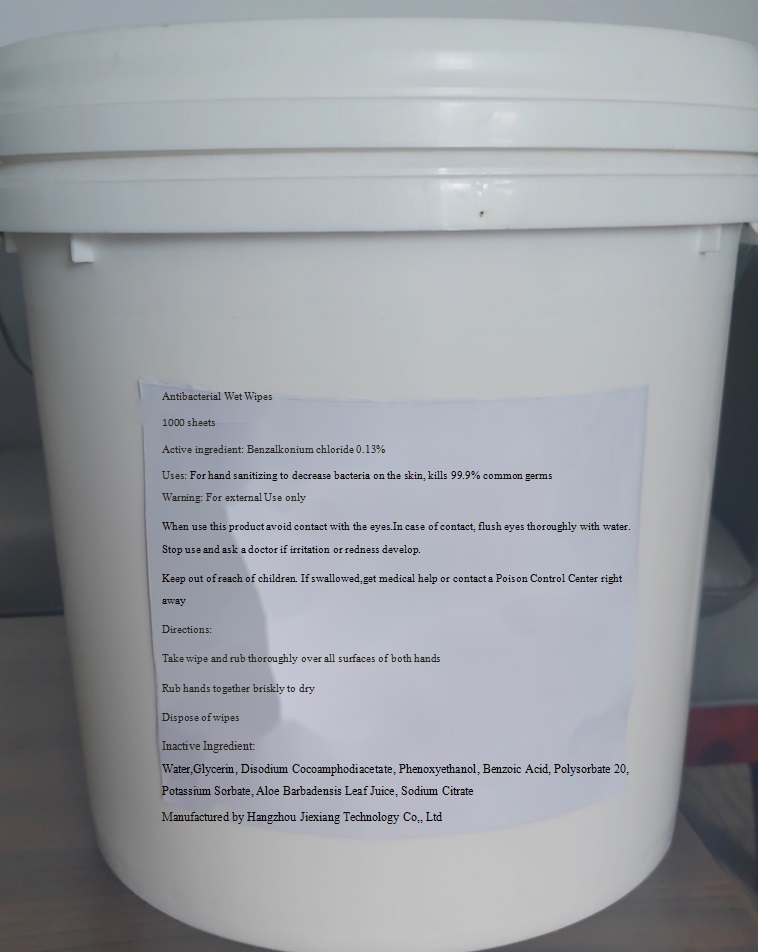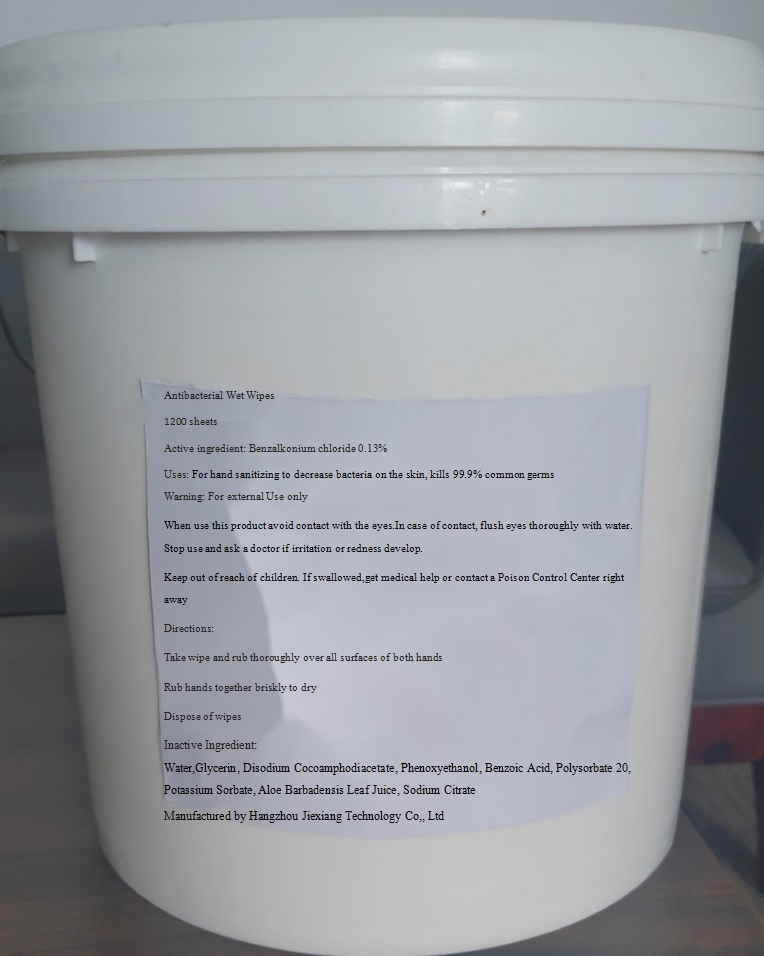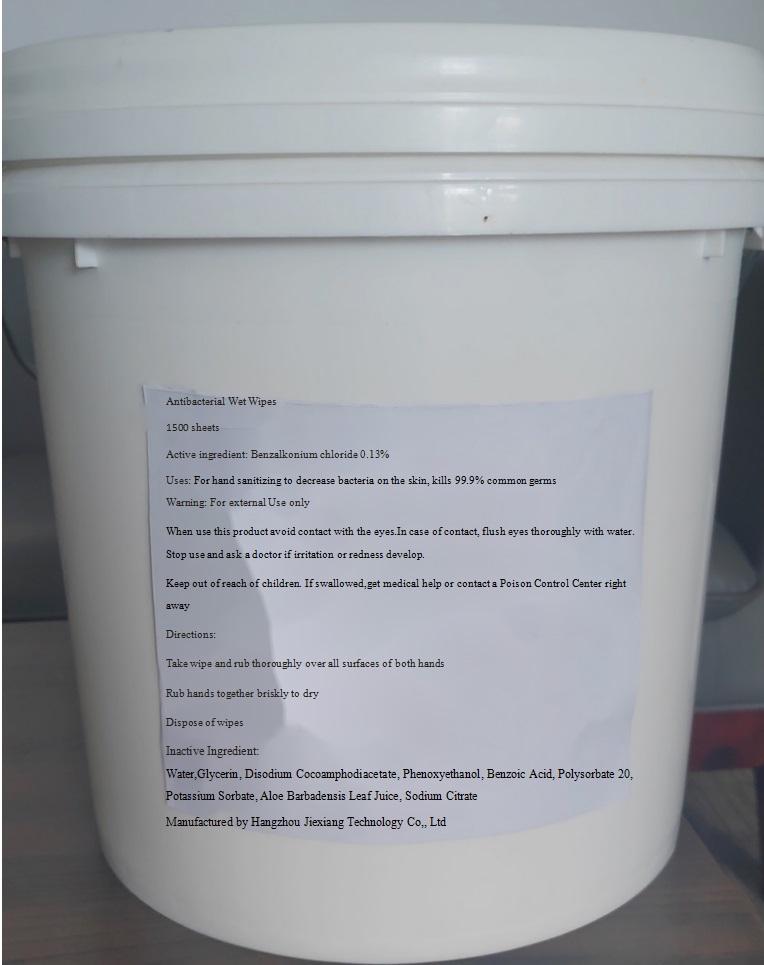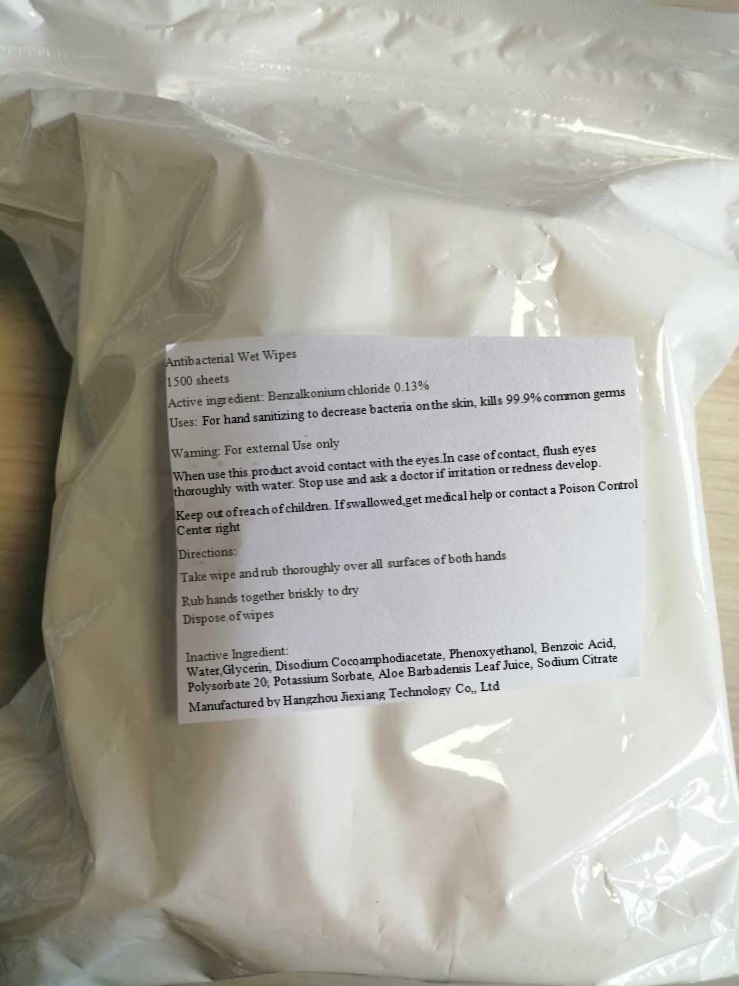 DRUG LABEL: Antibacterial Wet Wipes
NDC: 81991-002 | Form: CLOTH
Manufacturer: Antibacterial Wet Wipes
Category: otc | Type: HUMAN OTC DRUG LABEL
Date: 20220107

ACTIVE INGREDIENTS: BENZALKONIUM CHLORIDE 0.13 g/100 g
INACTIVE INGREDIENTS: ALOE VERA LEAF; WATER; DISODIUM COCOAMPHODIACETATE; PHENOXYETHANOL; BENZOIC ACID; GLYCERIN; POLYSORBATE 20; POTASSIUM SORBATE; SODIUM CITRATE

81991-002
Antibacterial Wipes

ACTIVE INGREDIENT

Benzalkonium chloride 0.13%

PURPOSE

Antibacterial Wet Wipes

INDICATIONS AND USAGE

For hand sanitizing to decrease bacteria on the skin,kills 99.9% common germs

WARNINGS

For external Use only

WHEN USING

When use this product avoid contact with the eyes.In case of contact, flush eyes thoroughly with water.

Stop use and ask a doctor if irritation or redness develop

Keep out of reach of children. If swallowed,get medical help or contact a Poison Control Center right away.

Directions

Take wipe and rub thoroughly over all surfaces of both hands

Rub hands together briskly to dry

Dispose of wipes

INACTIVE INGREDIENT

Water,Glycerin, Disodium Cocoamphodiacetate, Phenoxyethanol, Benzoic Acid, Polysorbate 20, Potassium Sorbate, Aloe Barbadensis Leaf Juice, Sodium Citrate